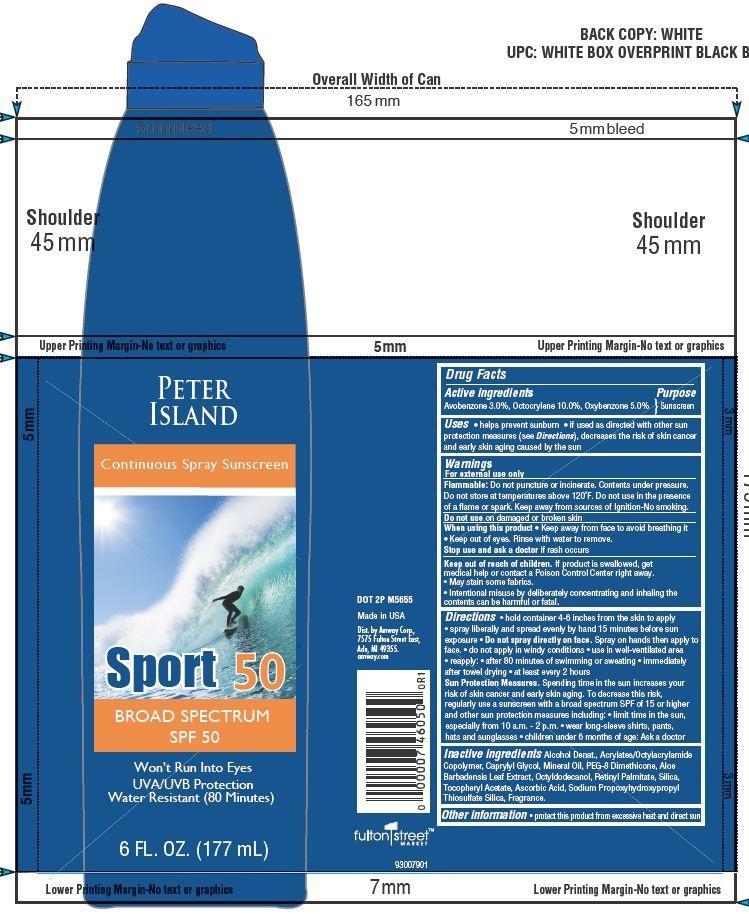 DRUG LABEL: Peter Island Continous sunscreen
NDC: 10056-709 | Form: SPRAY
Manufacturer: Access Business Group LLC
Category: otc | Type: HUMAN OTC DRUG LABEL
Date: 20130709

ACTIVE INGREDIENTS: OXYBENZONE 5 g/100 g; AVOBENZONE 3 g/100 g; OCTISALATE 5 g/100 g
INACTIVE INGREDIENTS: ALCOHOL; CAPRYLYL GLYCOL; MINERAL OIL; PEG-8 DIMETHICONE; ALOE VERA LEAF; OCTYLDODECANOL; VITAMIN A PALMITATE; SILICON DIOXIDE; .ALPHA.-TOCOPHEROL ACETATE; ASCORBIC ACID

Drug Facts

Active ingredients

Avobenzone 3.0%, Octocrylene 10.0%, Oxybenzone 5.0%

Purpose

Sunscreen

Warnings

For external use only
Flammable: Do not Puncture or incinerate, Contents under pressure.

Do not store at temperatures above 120 F. Do not use in the presence of a flame or spark. Keep away from sources of Ignition-No smoking.

Stop use and ask a doctor

if rash occurs

When using this product

- Keep away from face to avoid breaching it
- keep out of eyes
- Rinse with water to remove.

keep out of reach of children

if product is swallowed, get medical help or contact a Poison Control Center right away.

- May stain some fabrics.
- Intentional misuse by deliberately concentrating and inhaling the contents can be harmful or fatal.

DIRECTIONS:

- hold container 4-6 inches from the skin to apply
- spray liberally and spread evenlyb by hand 15 minutes before sun exposure
- Do not spray directly on face.
- Spray on hands then apply to face
- do not apply in windy conditionss
- use in well-ventiliated area
- reapply: after 80 minutes of swimming or sweating
- immediately after towel drying
- at least every 2 hours.

Sun protection measures:

- Spending time in the sun increase your risk of skin cancer and early skin aging To decrease this risk, regularly use a sunscreen with a broad spectrum SPF of 15 or higher and other sun protection measures including:
- limit time in the sun, especially from 10 a.m.- 2 p.m
- wear long -sleeve shirts, pants, hats and sunglasses
- children under 6 months of age:
- Ask a doctor

Other Information

protect this product from excessive heat and direct sun

Uses

- helps prevent sunburn
- if used as directed with other sun protection measures (see directions), decrease the risk of skin cancer and early skin aging caused by the sun.

Principal Display Panel

PETER

ISLAND

Continous Spray Sunscreen

Sport 50

BROAD SPECTRUM

SPF 50

Won't Run Into Eyes

UVA/UVB Protection

Water Resistant (80 Minutes)

6 FL.OZ. (177 mL)

Inactive Ingredients:

Alcohol decant, Acrylates/octylacrylamide Copolymer, Caprylyl Glycol, Mineral Oil, PEG_8 Dimethicone, Aloe Barbadensis Leaf Extract, Octyldodecanol, Retinyl Palmitate, Silica, Tocopheryl Leaf Extract, Ascorbic Acid, Sodium Propoxyhydroxypropyl Thiosulfate Silica, Fragrance.